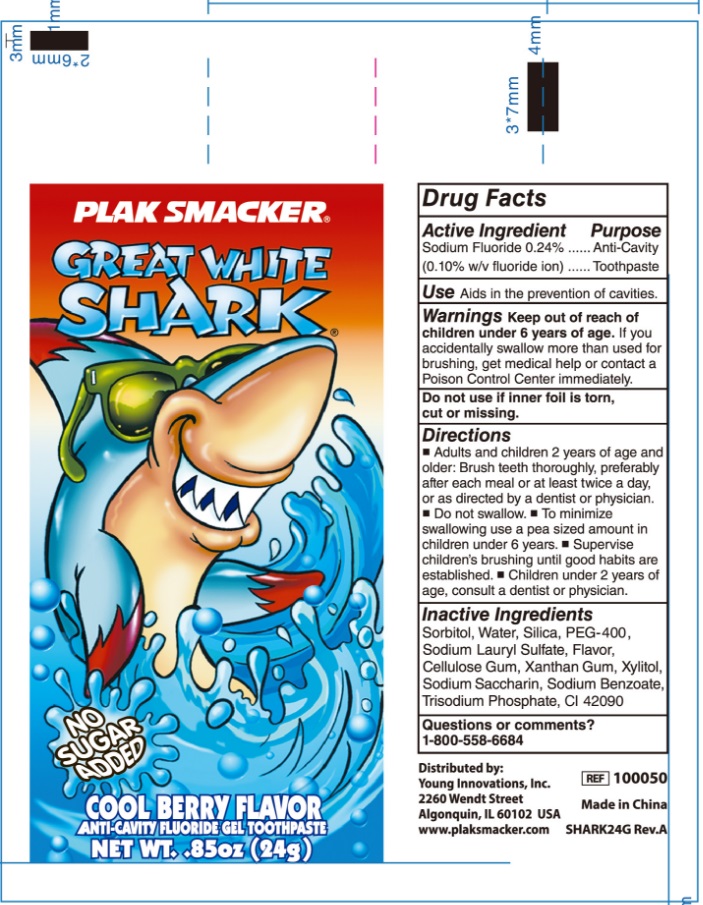 DRUG LABEL: Plak Smacker Great White Shark Cool Berry Flavor Anti Cavity Fluoride Gel Tooth
NDC: 85162-003 | Form: PASTE, DENTIFRICE
Manufacturer: Yangzhou ONE & ONLY Personal Care Products Co., LTD
Category: otc | Type: HUMAN OTC DRUG LABEL
Date: 20250116

ACTIVE INGREDIENTS: SODIUM FLUORIDE 0.1 g/100 g
INACTIVE INGREDIENTS: WATER; SORBITOL; HYDRATED SILICA; SODIUM LAURYL SULFATE; XANTHAN GUM; TRISODIUM PHOSPHIDE; SODIUM BENZOATE; XYLITOL; FD&C BLUE NO. 1; SACCHARIN SODIUM

85162-003

Active ingredients

SODIUM FLUORIDE 0.24% (0.11 w/v Fluoride ion)

<text xmlns="urn:hl7-org:v3"> <paragraph>SODIUM FLUORIDE 0.24%(0.11 w/v Fluoride ion)</paragraph> <paragraph/>&lt;text xmlns="urn:hl7-org:v3"> &lt;paragraph>SODIUM FLUORIDE 0.24%(0.11 w/v Fluoride ion)&lt;/paragraph> &lt;paragraph/>&amp;lt;text xmlns="urn:hl7-org:v3"> &amp;lt;paragraph>SODIUM FLUORIDE 0.24%(0.10 w/v Fluoride ion)&amp;lt;/paragraph> &amp;lt;paragraph/>&amp;amp;lt;text xmlns="urn:hl7-org:v3"> &amp;amp;lt;paragraph>SODIUM FLUORIDE 0.24%(0.10 w/v Fluoride ion)&amp;amp;lt;/paragraph> &amp;amp;lt;paragraph/>&amp;amp;amp;lt;text xmlns="urn:hl7-org:v3"> &amp;amp;amp;lt;paragraph>SODIUM FLUORIDE 0.24%(0.10 w/v Fluoride ion)&amp;amp;amp;lt;/paragraph> &amp;amp;amp;lt;paragraph/> &amp;amp;amp;lt;/text>&amp;amp;lt;/text>&amp;lt;/text>&lt;/text></text>

Purpose

Anti-cavity toothpaste

Uses

Aids in the prevention of cavities.

Warnings

Keep out of the reach of children under 6 years of age. If you accidently swallow more than used for brushing,get medical help or contact a Poison Control Center immediately.

Do not use if the inner foil is torn, cut, or missing

Keep out of reach of children.

Directions

- Adults and children 2 years of age and older: Brush teeth thoroughly, preferrably after each meal or at least twice a day, or as directed by a dentist or a physician
- Do not swallow
- To minimize wallowing, use a pea sizes amount in children under 6 years
- Supervise children's brushing until good habits are established
- Children under 2 years of age: consult a dentist or physician

INACTIVE INGREDIENT

Sorbitol, Water, Silica, PEG-400, Sodium lauryl sulfate, Cellulose gum, Xanthan gum, flavor, Xylitol, Sodium sacharine, Sodium benzoate, Trisodium phosphate, CI 42090